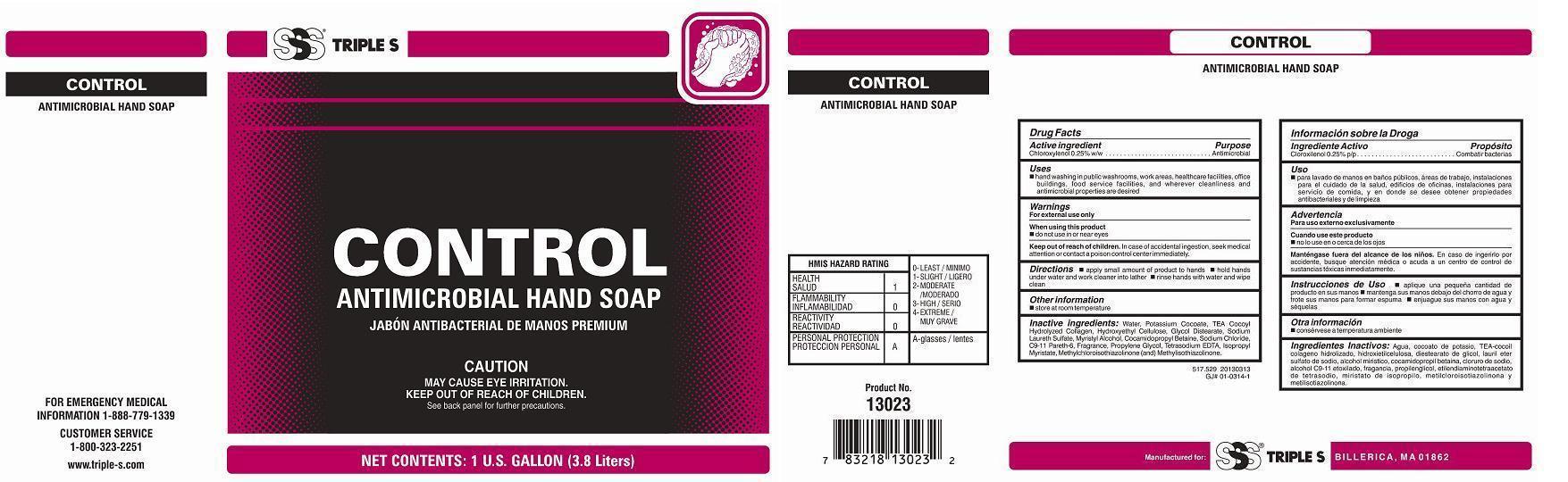 DRUG LABEL: CONTROL
NDC: 59110-517 | Form: SOAP
Manufacturer: Standardized Sanitation Systems
Category: otc | Type: HUMAN OTC DRUG LABEL
Date: 20180207

ACTIVE INGREDIENTS: CHLOROXYLENOL 2.5 g/1000 mL
INACTIVE INGREDIENTS: WATER; METHYLCHLOROISOTHIAZOLINONE; METHYLISOTHIAZOLINONE; HYDROXYETHYL CELLULOSE (5000 MPA.S AT 1%); POTASSIUM COCOATE; EDETATE SODIUM; GLYCOL DISTEARATE; SODIUM LAURETH SULFATE; MYRISTYL ALCOHOL; COCAMIDOPROPYL BETAINE; SODIUM CHLORIDE; PROPYLENE GLYCOL; ISOPROPYL MYRISTATE; C9-11 PARETH-6

Active ingredient

Chloroxylenol 0.25% w/w

Purpose

Antimicrobial

Keep out of reach of children

In case of accidental ingestion, seek medical attention or contact a poison control center immediately.

Uses

Hand washing in public washrooms, work areas, healthcare facilities, office buildings, food

service facilities, and wherever cleanliness and antimicrobial properties are desired

Warnings

For external use only

When using this product

- do not use in or near eyes

Directions

 Apply small amount of product to hands

 Hold hands under water and work cleaner into lather

 Rinse hands with water and wipe clean

Other information

 store at room temperature

Inactive ingredients:

Water, Potassium Cocoate, TEA-Cocoyl Hydrolyzed Collagen, Hydroxyethyl Cellulose, Glycol Distearate, Sodium Laureth Sulfate, Myristyl Alcohol, Cocoamidopropyl Betaine, Sodium Chloride, C9-11 Pareth-6, Fragrance, Propylene Glycol, Tetrasodium EDTA, Isopropyl Myristate, Methylchloroisothiazolinone (and) Methylisothiazolinone.